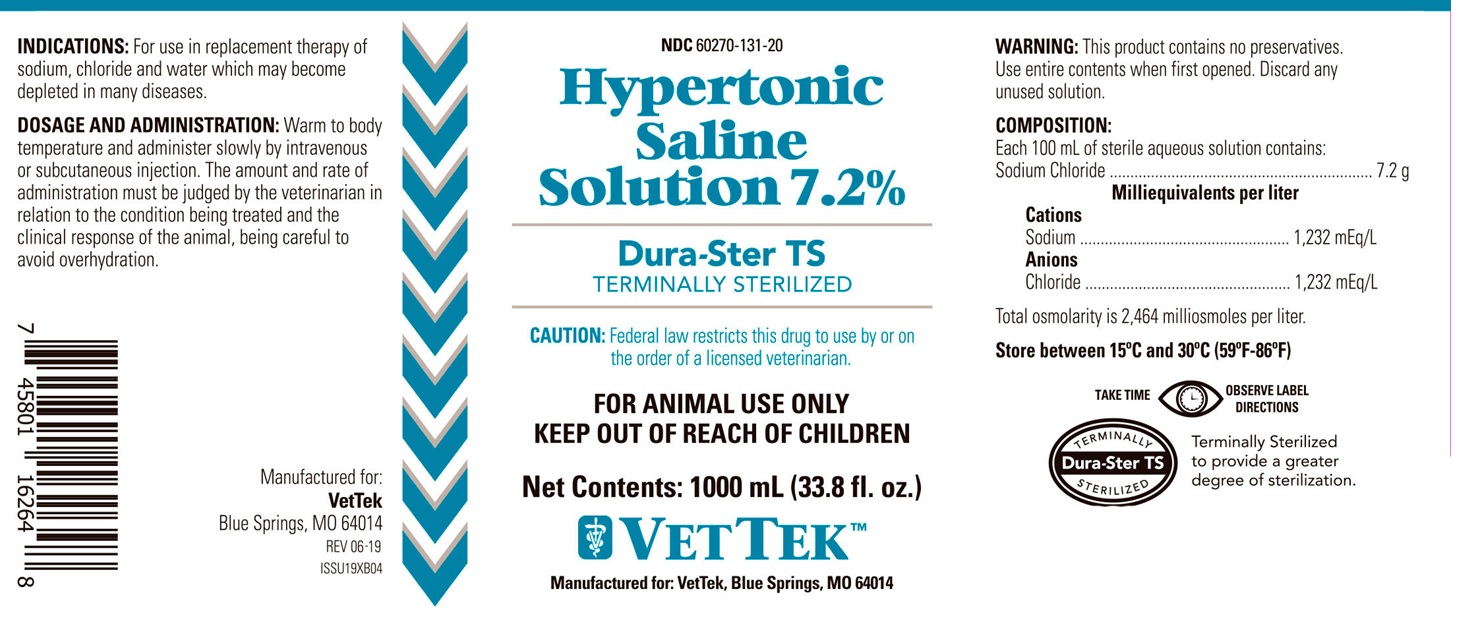 DRUG LABEL: Hypertonic Saline
NDC: 60270-131 | Form: INJECTION, SOLUTION
Manufacturer: VetTek
Category: animal | Type: PRESCRIPTION ANIMAL DRUG LABEL
Date: 20191101

ACTIVE INGREDIENTS: SODIUM CHLORIDE 7.2 g/100 mL

HYPERTONIC SALINE SOLUTION 7.2%

INDICATIONS:

For use in replacement therapy of sodium, chloride and water which may become depleted in many diseases.

CAUTION:

This product contains no preservatives. Use entire contents when first opened. Discard any unused solution.

DOSAGE AND ADMINISTRATION:

Warm to body temperature and administer slowly by intravenous or subcutaneous injection. The amount and rate of administration must be
judged in relation to the condition being treated and the clinical response of the animal, being careful to avoid overhydration.

VETERINARY INDICATIONS

For Animal Use Only

KEEP OUT OF REACH OF CHILDREN

CAUTION:

Federal law restricts this drug to use by or on the order of a licensed veterinarian.

COMPOSITION:

Each 100 mL of sterile aqueous solution contains:
Sodium Chloride ................... 7.2 g

Milliequivalents per liter

Cations
Sodium ......................... 1232 mEq/L
Anions
Chloride ........................ 1232 mEq/L

Total osmolarity is 2464 milliosmoles per liter.

STORAGE AND HANDLING

Store between 15°C and 30°C (59°F and 86°F)

GENERAL PRECAUTIONS

TAKE TIME OBSERVE LABEL DIRECTIONS

INFORMATION FOR OWNERS/CAREGIVERS

Manufactured for:

VETTEK
Blue Springs, MO 64014
REV 06-19
ISSU19XB04

PACKAGE LABEL

NDC 60270-131-20

Hypertonic Saline Solution 7.2%

Durs-Ster TS

TERMINALLY STERILIZED

Net Contents: 1000 mL (33.8 fl. oz.)